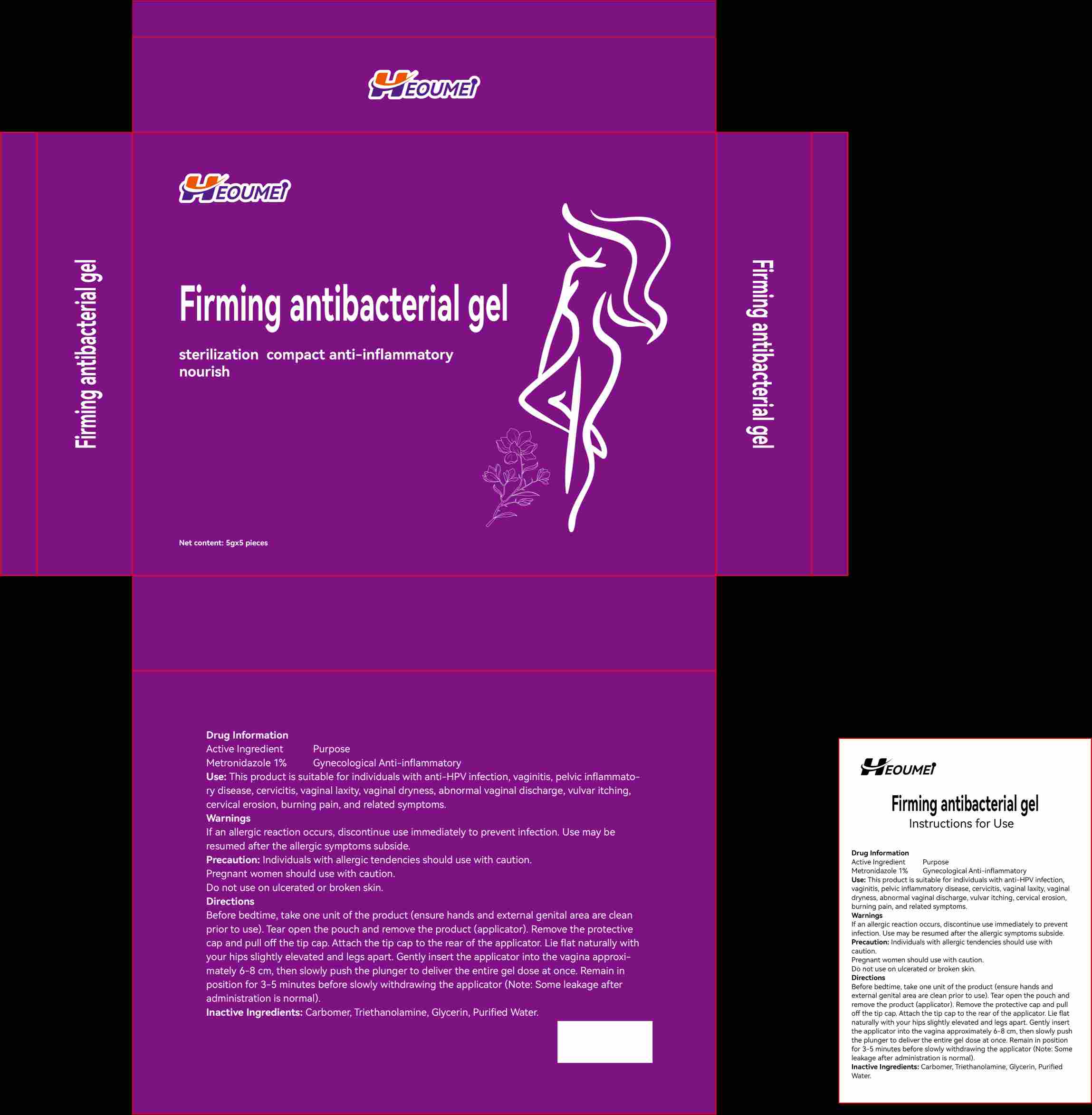 DRUG LABEL: Firming antibacterial
NDC: 87365-362 | Form: GEL
Manufacturer: Jiangxi He-Oumei Health Industry Co., Ltd.
Category: homeopathic | Type: HUMAN OTC DRUG LABEL
Date: 20260124

ACTIVE INGREDIENTS: METRONIDAZOLE 1 g/1 1
INACTIVE INGREDIENTS: CARBOMER 940; WATER; TRIETHANOLAMINE

ACTIVE INGREDIENT

Metronidazole

PURPOSE

Antibacterial and anti-inflammatory

keep out of reach of children section

keep out of reach of children section

INDICATIONS AND USAGE

Antibacterial and anti-inflammatory

DOSAGE AND ADMINISTRATION

Apply to the affected area to reduce inflammation

INACTIVE INGREDIENT

Carbomer 940,Triethanolamine,Glycerol,Water